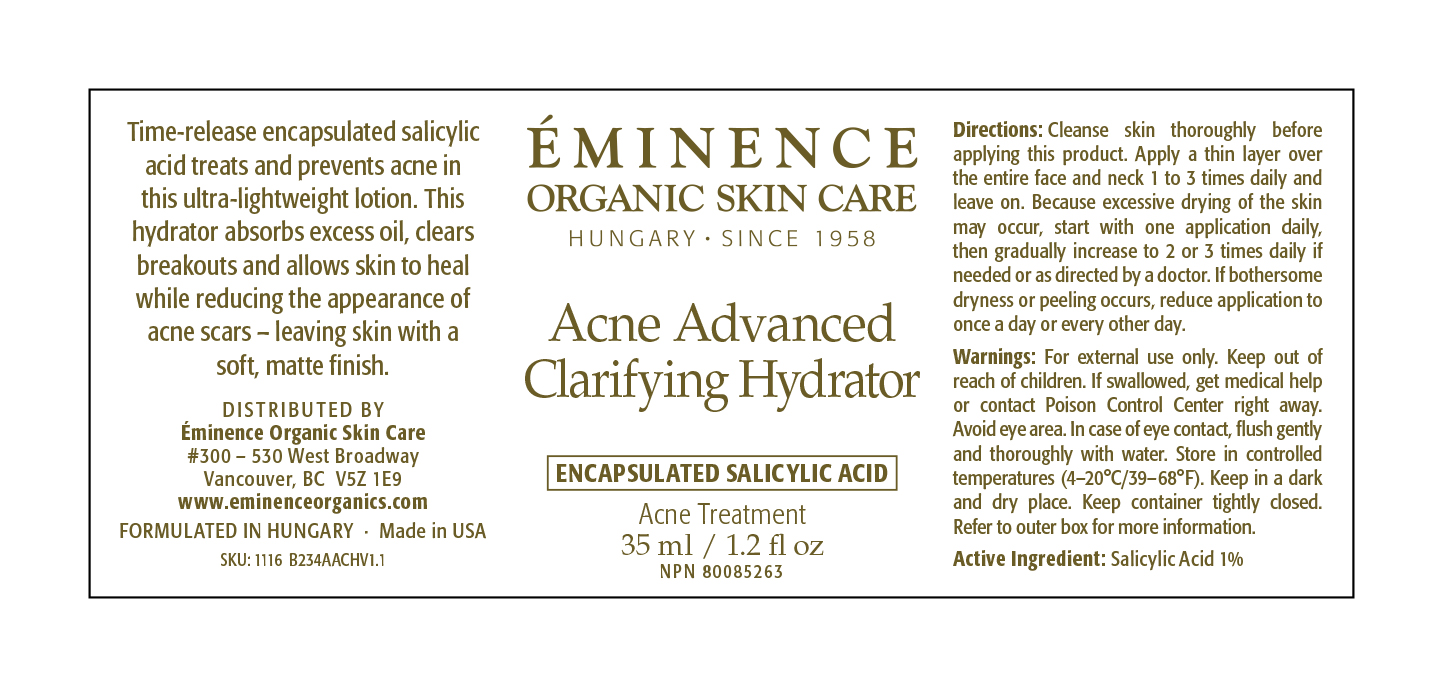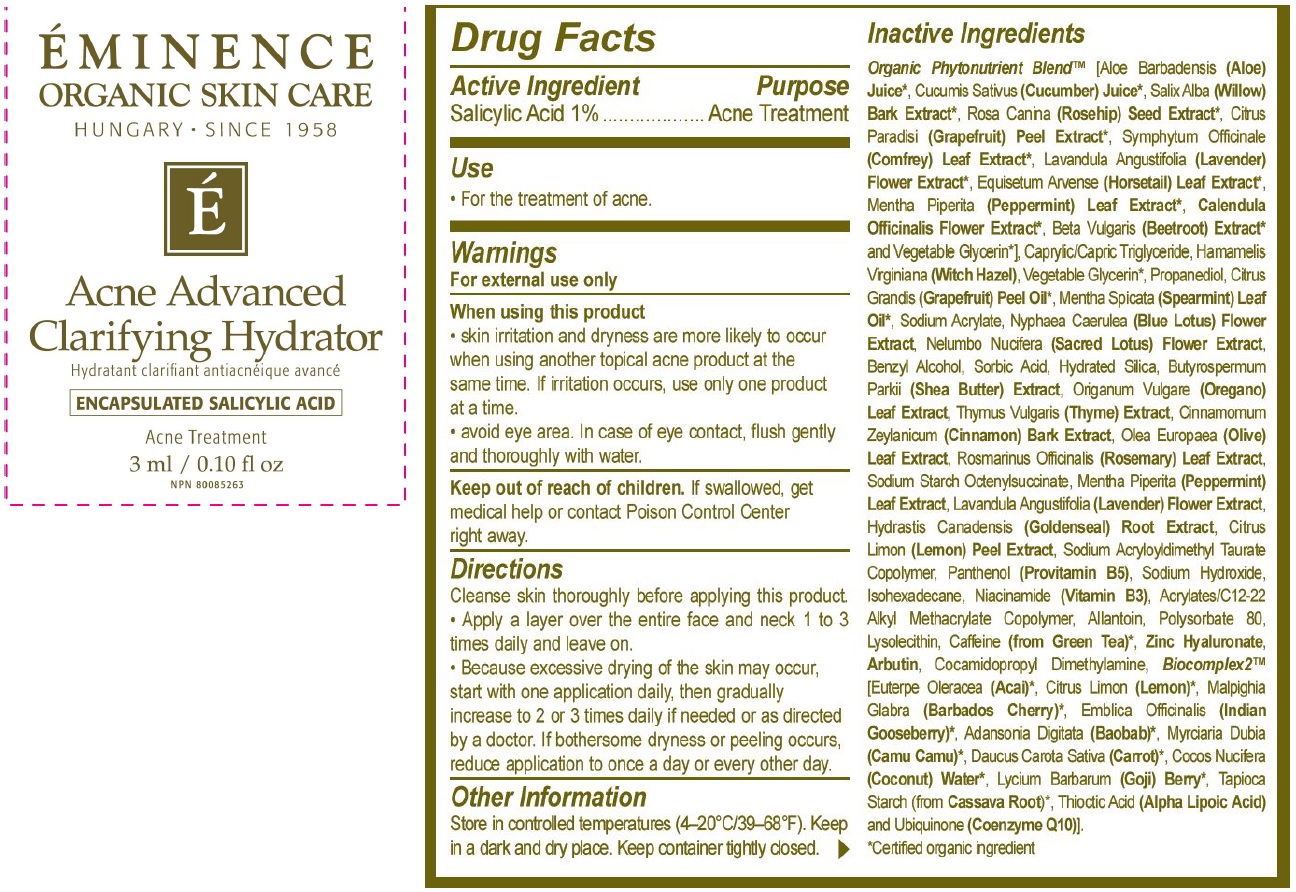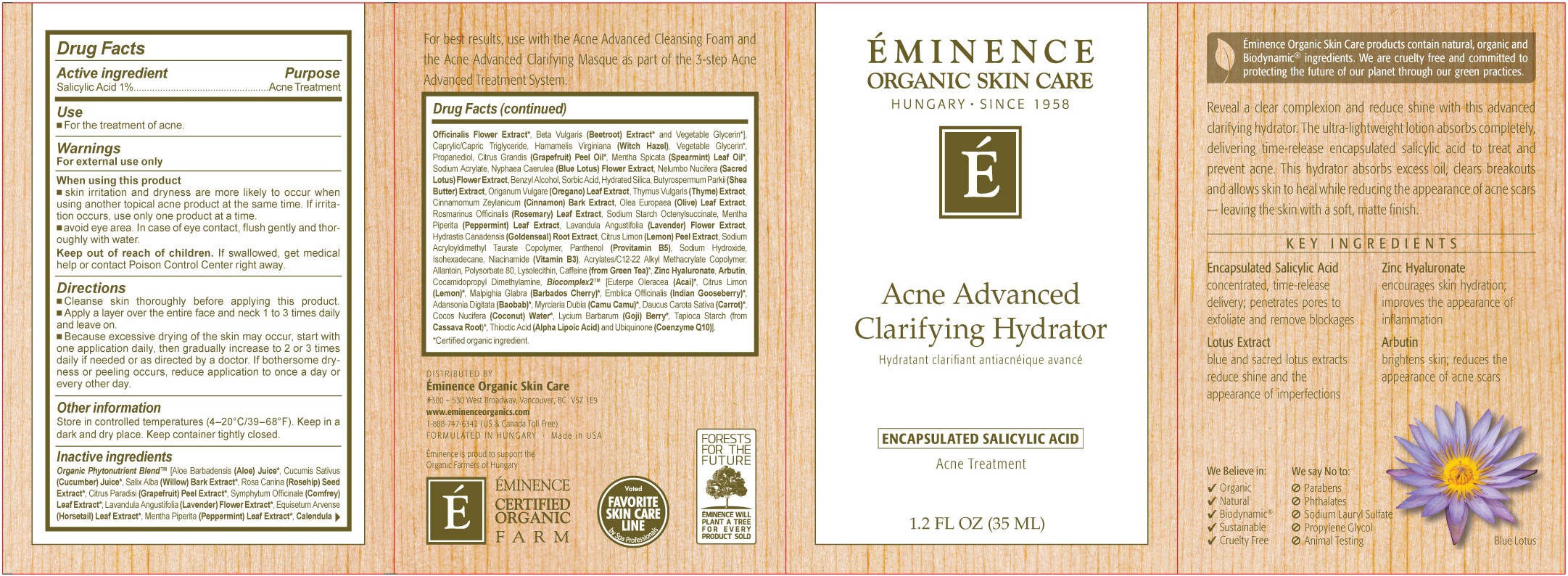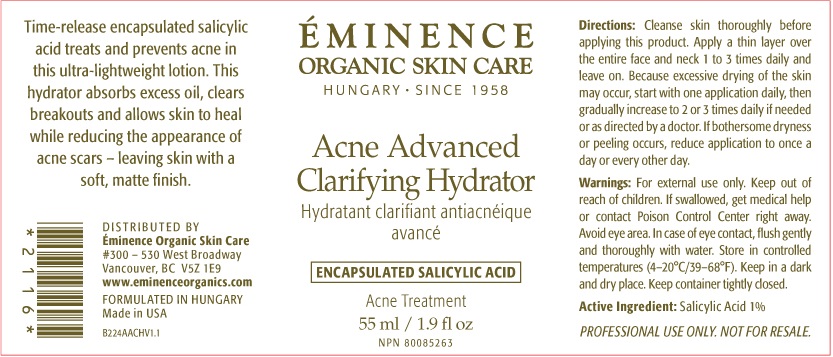 DRUG LABEL: Acne Advanced Clarifying Hydrator
NDC: 15751-3030 | Form: CREAM
Manufacturer: Eminence Organic Skin Care Ltd.
Category: otc | Type: HUMAN OTC DRUG LABEL
Date: 20231208

ACTIVE INGREDIENTS: SALICYLIC ACID 10 mg/1 mL
INACTIVE INGREDIENTS: ALOE; CUCUMBER; ROSA MOSCHATA OIL; GRAPEFRUIT; SYMPHYTUM UPLANDICUM LEAF; PEPPERMINT; CALENDULA OFFICINALIS FLOWER; BETA VULGARIS; GLYCERIN; MEDIUM-CHAIN TRIGLYCERIDES; HAMAMELIS VIRGINIANA ROOT BARK/STEM BARK; PROPANEDIOL; CITRUS MAXIMA FRUIT RIND OIL; SPEARMINT; SODIUM ACRYLATE; OREGANO; THYME; CINNAMON; OLIVE OIL; ROSEMARY; GOLDENSEAL; LEMON; DEXPANTHENOL; SODIUM HYDROXIDE; ISOHEXADECANE; NIACIN; ALLANTOIN; POLYSORBATE 80; LYSOPHOSPHATIDYLCHOLINE, SOYBEAN; GREEN TEA LEAF; ARBUTIN; COCAMIDOPROPYL DIMETHYLAMINE; SOYBEAN OIL; BENZYL ALCOHOL; SUNFLOWER OIL; SORBIC ACID; SODIUM POLYACRYLATE (2500000 MW); ACAI; CARROT; COCONUT; STARCH, TAPIOCA; THIOCTIC ACID; UBIDECARENONE

Acne Advanced Clarifying Hydrator

Active ingredient

Salicylic Acid 1%

Purpose

Acne Treatment

Use

- For the treatment of acne.

Warnings

For external use only

When using this product

- Skin irritation and dryness are more likely to occur when using another topical acne product at the same time. if irritation occurs, use only one product at a time.
- avoid eye area. In case of eye contact, flush gently and thoroughly with water.

Keep out of reach of children.

If swallowed, get medical help or contaact Poison Control Center right away.

Direcitons

- Cleanse skin thoroughly before applying this product
- Apply a layer over the entire face and neck 1 to 3 times daily and leave on.
- Because excessive drying of the skin may occur, start with one application daily, then gradually increase to 2 ot 3 times daily if needed or as directed by a doctor. If bothersome dryness or peeling occurs, reduce application to once a day or every other day.

Other information

Store in controlled temperatures (4-20°C/39-68°F). Keep in a dark and dry place. Keep container tightly closed.

Inactive ingredients

Organic Phytonutrient Blend (Aloe Barbadensis (Aloe) Juice, Cucumis Sativus (Cucumber) Juice, Salix Alba (Willow) Bark Extract, Rosa Canina (Rosehip) Seed Extract, Citrus Paradisi (Grapefruit) Peel Extract, Symphytum Officinale (Comfrey) Leaf Extract, Lavandula Angustifolia (Lavender) Flower Extract, Equisetum Argense (Horsetail Leaf Extract, Mentha Piperita (Peppermint) Leaf Extract, Calendula Officinalis Flower Extract, Beta Vulgaris (Beetroot) Extract and Vegetable Glycerin], Caprylic/Capric Triglyceride, Hamamelis Virginiana (Witch Hazel), Vegetable Glycerin, Propanediol, Citrus Grandis (Grapefruit) Peel Oil, Mentha Spicata (Spearmint) Leaf Oil, Sodium Acrylate, Nyphaea Caerulea (Blue Lotus) Flower Extract, Nelumbo Nucifera (Sacred Lotus) Flower Extract, Origanum Vulgare (Oregano) Leaf Extract, Thymus Vulgaris (Thyme) Extract, Cinnamomum Zeylanium (Cinnamon) Bark Extract, Olea Europaea (Olive) Leaf Extract, Rosmarinus Officinalis (Rosemary) Leaf Extract, Sodium Starch Octenylsuccinate, Mentha Piperita (Peppermint) Leaf Extract, Lavandula Angustifolia (Lavender) Flower Extract, Hydrastis Canadensis (Goldenseal) Root Extract, Citrus Limon (Lemon) Peel Extract, Sodium Acrylolydimethyl Taurate Copolymer, Panthenol (Provitamin B5), Sodium Hydroxide, Isohexadecane, Niacinamide (Vitamin B3), Acrylates/C12-22 Alkyl Methacrylate Copolymer, Allantoin, Polysorbate 80, Lysolecithin, Caffeine (from Green Tea), Zinc Hyaluronate, Arbutin, Cocamidopropyl Dimethylamine, Biocomplex2 [Euterpe Oleracea (Acai), [Euterpe Oleracea (Acai), Citrus Limon (Lemon), Malpighia Glabra (Barbados Cherry), Emblica Officinalis (Indian Gooseberry), Adansonia Digitata (Baobab), Myrciaria Dubia (Camu Camu), Daucus Carota Sativa (Carrot), Cocos Nucifera (Coconut) Water, Lycium Barbarum (Goji) Berry, Tapioca Starch (from Cassave Root), Thioctic Acid (Alpha Lipoic Acid) and Ubiquinone (Coenzyme Q10)

*Certified organic ingredient